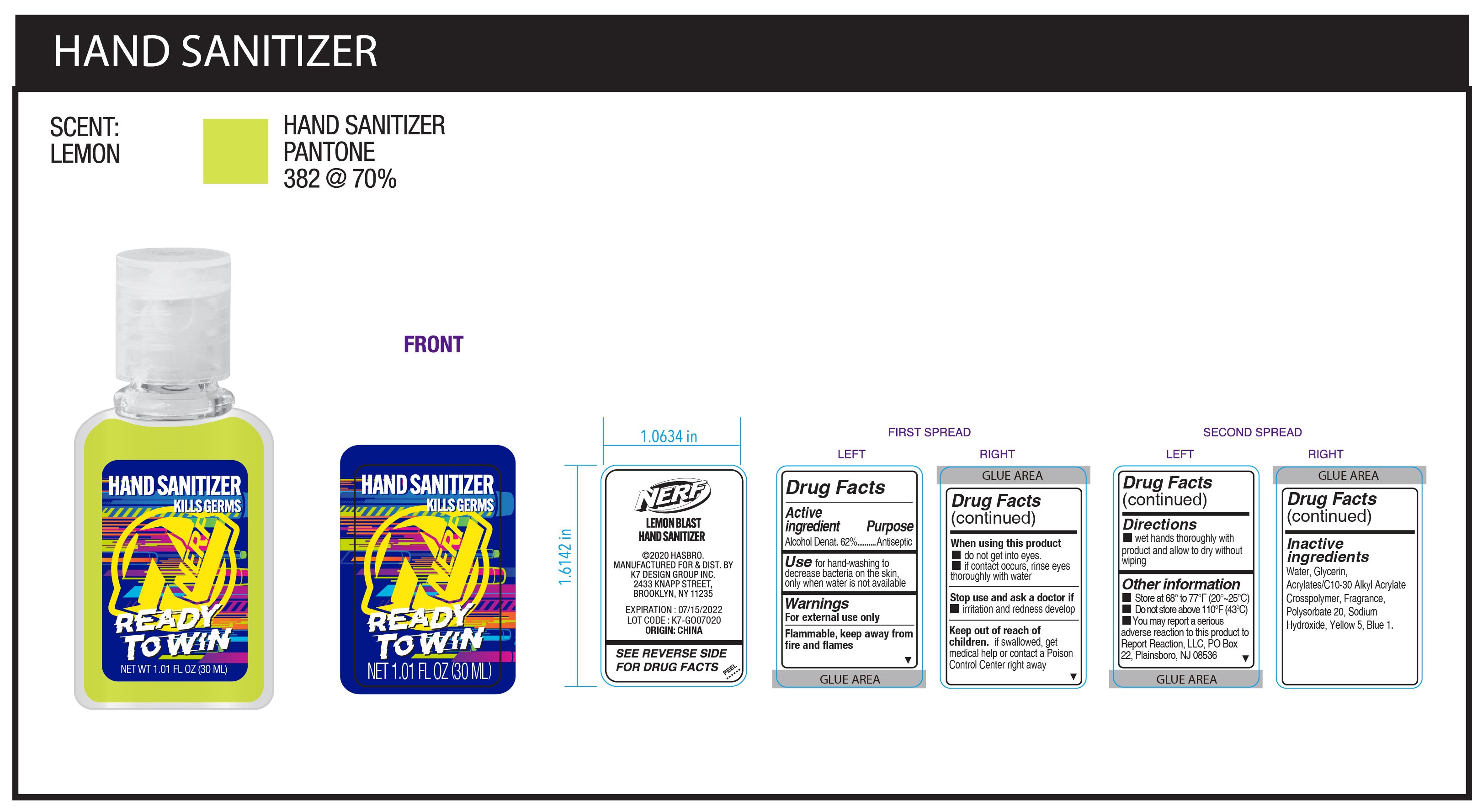 DRUG LABEL: NERF Hand Sanitizer
NDC: 51522-030 | Form: GEL
Manufacturer: Gold Orient International Limited
Category: otc | Type: HUMAN OTC DRUG LABEL
Date: 20200723

ACTIVE INGREDIENTS: ALCOHOL 62 mL/100 mL
INACTIVE INGREDIENTS: POLYSORBATE 20; GLYCERIN; CARBOMER COPOLYMER TYPE A (ALLYL PENTAERYTHRITOL CROSSLINKED); WATER; FD&C BLUE NO. 1; SODIUM HYDROXIDE; FD&C YELLOW NO. 5

Nerf (NRF 100)

Active Ingredient(s)

Alcohol 62% v/v.

Purpose

Antiseptic

Use

For hand-washing to decrease bacteria on the skin, only when water is not available

Warnings

For external use only. Flammable. Keep away from heat or flame

Do not use

- in children less than 2 months of age
- on open skin wounds

WHEN USING

- Do not get into eyes.
- if contact occurs, rinse eyes thoroughly with water

STOP USE

irritation and redness develop

Keep out of reach of children. If swallowed, get medical help or contact a Poison Control Center right away.

Directions

- wet hands thoroughly with product and allow to dry without wiping

Other information

- Store between 66 to 77F (20-25C)
- Do not store above 110F (43C)
- You may report a serious adverse reaction to this product to Report Reaction, LLC, PO Box 22 Plainsboro, NJ 08536

Inactive ingredients

Water, Glycerin, Acrylates/ C10-30 Alkyl Acrylates Crosspolymer, Fragrance, Polysorbate 20, Sodium Hydroxide, Yellow 5, Blue 1